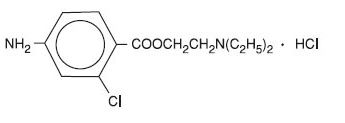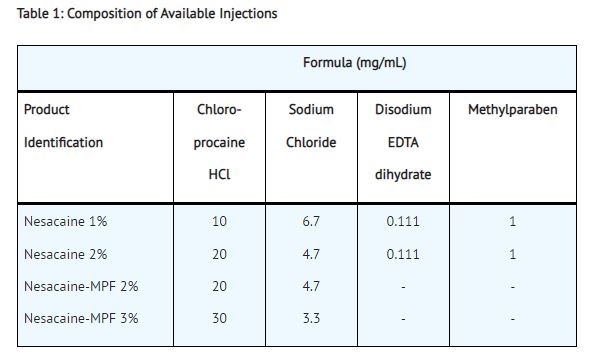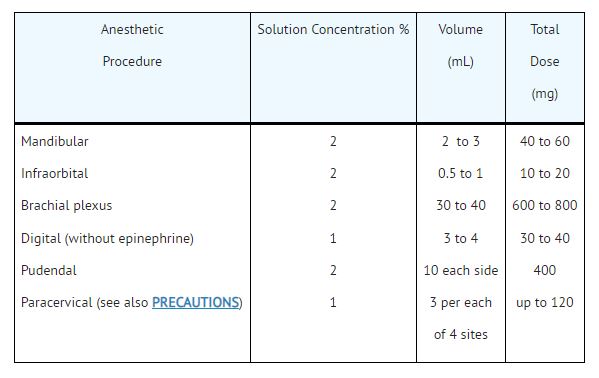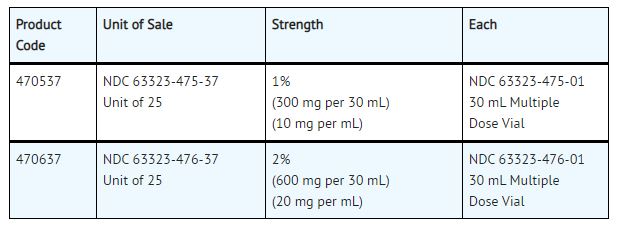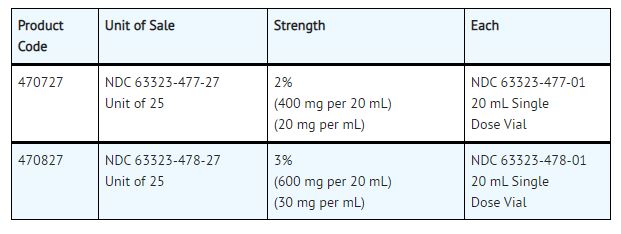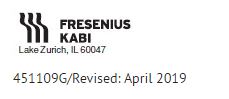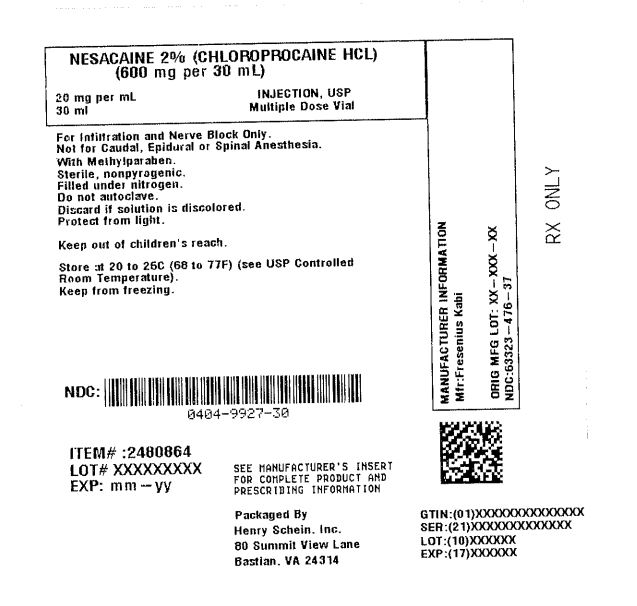 DRUG LABEL: NESACAINE
NDC: 0404-9927 | Form: INJECTION, SOLUTION
Manufacturer: Henry Schein, Inc.
Category: prescription | Type: HUMAN PRESCRIPTION DRUG LABEL
Date: 20241014

ACTIVE INGREDIENTS: CHLOROPROCAINE HYDROCHLORIDE 20 mg/1 mL
INACTIVE INGREDIENTS: SODIUM CHLORIDE 4.7 mg/1 mL; EDETATE DISODIUM 0.111 mg/1 mL; METHYLPARABEN 1 mg/1 mL; SODIUM HYDROXIDE; HYDROCHLORIC ACID

451109G /Revised: April 2019
Nesacaine®
Nesacaine®- MPF
Nesacaine®
(chloroprocaine HCl injection, USP)
Nesacaine®- MPF
(chloroprocaine HCl injection, USP)
For Infiltration and Nerve Block

DESCRIPTION:

Nesacaine and Nesacaine-MPF Injections are sterile non-pyrogenic local anesthetics. The active ingredient in Nesacaine and Nesacaine-MPF Injections is chloroprocaine HCl (benzoic acid, 4-amino-2-chloro-2-(diethylamino) ethyl ester, monohydrochloride), which is represented by the following structural formula:

The solutions are adjusted to pH 2.7 to 4.0 by means of sodium hydroxide and/or hydrochloric acid. Filled under nitrogen.

Nesacaine and Nesacaine-MPF Injections should not be resterilized by autoclaving.

CLINICAL PHARMACOLOGY:

Chloroprocaine, like other local anesthetics, blocks the generation and the conduction of nerve impulses, presumably by increasing the threshold for electrical excitation in the nerve, by slowing the propagation of the nerve impulse and by reducing the rate of rise of the action potential. In general, the progression of anesthesia is related to the diameter, myelination and conduction velocity of affected nerve fibers. Clinically, the order of loss of nerve function is as follows: (1) pain, (2) temperature, (3) touch, (4) proprioception, and (5) skeletal muscle tone.

Systemic absorption of local anesthetics produces effects on the cardiovascular and central nervous systems. At blood concentrations achieved with normal therapeutic doses, changes in cardiac conduction, excitability, refractoriness, contractility, and peripheral vascular resistance are minimal. However, toxic blood concentrations depress cardiac conduction and excitability, which may lead to atrioventricular block and ultimately to cardiac arrest. In addition, with toxic blood concentrations myocardial contractility may be depressed and peripheral vasodilation may occur, leading to decreased cardiac output and arterial blood pressure.

Following systemic absorption, toxic blood concentrations of local anesthetics can produce central nervous system stimulation, depression, or both. Apparent central stimulation may be manifested as restlessness, tremors and shivering, which may progress to convulsions. Depression and coma may occur, possibly progressing ultimately to respiratory arrest.

However, the local anesthetics have a primary depressant effect on the medulla and on higher centers. The depressed stage may occur without a prior stage of central nervous system stimulation.

PHARMACOKINETICS:

The rate of systemic absorption of local anesthetic drugs is dependent upon the total dose and concentration of drug administered, the route of administration, the vascularity of the administration site, and the presence or absence of epinephrine in the anesthetic injection. Epinephrine usually reduces the rate of absorption and plasma concentration of local anesthetics and is sometimes added to local anesthetic injections in order to prolong the duration of action.

The onset of action with chloroprocaine is rapid (usually within 6 to 12 minutes), and the duration of anesthesia, depending upon the amount used and the route of administration, may be up to 60 minutes.

Local anesthetics appear to cross the placenta by passive diffusion. However, the rate and degree of diffusion varies considerably among the different drugs as governed by: (1) the degree of plasma protein binding, (2) the degree of ionization, and (3) the degree of lipid solubility. Fetal/maternal ratios of local anesthetics appear to be inversely related to the degree of plasma protein binding, since only the free, unbound drug is available for placental transfer. Thus, drugs with the highest protein binding capacity may have the lowest fetal/maternal ratios. The extent of placental transfer is also determined by the degree of ionization and lipid solubility of the drug. Lipid soluble, nonionized drugs readily enter the fetal blood from the maternal circulation.

Depending upon the route of administration, local anesthetics are distributed to some extent to all body tissues, with high concentrations found in highly perfused organs such as the liver, lungs, heart, and brain.

Various pharmacokinetic parameters of the local anesthetics can be significantly altered by the presence of hepatic or renal disease, addition of epinephrine, factors affecting urinary pH, renal blood flow, the route of administration, and the age of the patient. The in vitro plasma half-life of chloroprocaine in adults is 21 ± 2 seconds for males and 25 ± 1 seconds for females. The in vitro plasma half-life in neonates is 43 ± 2 seconds.

Chloroprocaine is rapidly metabolized in plasma by hydrolysis of the ester linkage by pseudocholinesterase. The hydrolysis of chloroprocaine results in the production of ß-diethylaminoethanol and 2-chloro-4-aminobenzoic acid, which inhibits the action of the sulfonamides (see PRECAUTIONS).

The kidney is the main excretory organ for most local anesthetics and their metabolites. Urinary excretion is affected by urinary perfusion and factors affecting urinary pH.

INDICATIONS AND USAGE:

Nesacaine 1% and 2% Injections, in multidose vials with methylparaben as preservative, are indicated for the production of local anesthesia by infiltration and peripheral nerve block. They are not to be used for lumbar or caudal epidural anesthesia.

Nesacaine-MPF 2% and 3% Injections, in single dose vials without preservative and without EDTA, are indicated for the production of local anesthesia by infiltration, peripheral and central nerve block, including lumbar and caudal epidural blocks.

Nesacaine and Nesacaine-MPF Injections are not to be used for subarachnoid administration.

CONTRAINDICATIONS:

Nesacaine and Nesacaine-MPF Injections are contraindicated in patients hypersensitive (allergic) to drugs of the PABA ester group.

Lumbar and caudal epidural anesthesia should be used with extreme caution in persons with the following conditions: existing neurological disease, spinal deformities, septicemia, and severe hypertension.

WARNINGS:

LOCAL ANESTHETICS SHOULD ONLY BE EMPLOYED BY CLINICIANS WHO ARE WELL VERSED IN DIAGNOSIS AND MANAGEMENT OF DOSE RELATED TOXICITY AND OTHER ACUTE EMERGENCIES WHICH MIGHT ARISE FROM THE BLOCK TO BE EMPLOYED, AND THEN ONLY AFTER ENSURING THE IMMEDIATE AVAILABILITY OF OXYGEN, OTHER RESUSCITATIVE DRUGS, CARDIOPULMONARY RESUSCITATIVE EQUIPMENT, AND THE PERSONNEL RESOURCES NEEDED FOR PROPER MANAGEMENT OF TOXIC REACTIONS AND RELATED EMERGENCIES (see also ADVERSE REACTIONS and PRECAUTIONS). DELAY IN PROPER MANAGEMENT OF DOSE RELATED TOXICITY, UNDERVENTILATION FROM ANY CAUSE AND/OR ALTERED SENSITIVITY MAY LEAD TO THE DEVELOPMENT OF ACIDOSIS, CARDIAC ARREST AND, POSSIBLY, DEATH. NESACAINE (chloroprocaine HCl Injection, USP) contains methylparaben and should not be used for lumbar or caudal epidural anesthesia because safety of this antimicrobial preservative has not been established with regard to intrathecal injection, either intentional or unintentional. NESACAINE-MPF Injection contains no preservative; discard unused injection remaining in vial after initial use.

Intra-articular infusions of local anesthetics following arthroscopic and other surgical procedures is an unapproved use, and there have been post-marketing reports of chondrolysis in patients receiving such infusions. The majority of reported cases of chondrolysis have involved the shoulder joint; cases of gleno-humeral chondrolysis have been described in pediatric and adult patients following intra-articular infusions of local anesthetics with and without epinephrine for periods of 48 to 72 hours. There is insufficient information to determine whether shorter infusion periods are not associated with these findings. The time of onset of symptoms, such as joint pain, stiffness and loss of motion can be variable, but may begin as early as the 2nd month after surgery. Currently, there is no effective treatment for chondrolysis; patients who experienced chondrolysis have required additional diagnostic and therapeutic procedures and some required arthroplasty or shoulder replacement.

Vasopressors should not be used in the presence of ergot-type oxytocic drugs, since a severe persistent hypertension may occur.

To avoid intravascular injection, aspiration should be performed before the anesthetic solution is injected. The needle must be repositioned until no blood return can be elicited. However, the absence of blood in the syringe does not guarantee that intravascular injection has been avoided.

Mixtures of local anesthetics are sometimes employed to compensate for the slower onset of one drug and the shorter duration of action of the second drug. Experiments in primates suggest that toxicity is probably additive when mixtures of local anesthetics are employed, but some experiments in rodents suggest synergism. Caution regarding toxic equivalence should be exercised when mixtures of local anesthetics are employed.

Methemoglobinemia

Cases of methemoglobinemia have been reported in association with local anesthetic use. Although all patients are at risk for methemoglobinemia, patients with glucose- 6-phosphate dehydrogenase deficiency, congenital or idiopathic methemoglobinemia, cardiac or pulmonary compromise, infants under 6 months of age, and concurrent exposure to oxidizing agents or their metabolites are more susceptible to developing clinical manifestations of the condition. If local anesthetics must be used in these patients, close monitoring for symptoms and signs of methemoglobinemia is recommended.

Signs of methemoglobinemia may occur immediately or may be delayed some hours after exposure, and are characterized by a cyanotic skin discoloration and/or abnormal coloration of the blood. Methemoglobin levels may continue to rise; therefore, immediate treatment is required to avert more serious central nervous system and cardiovascular adverse effects, including seizures, coma, arrhythmias, and death. Discontinue NESACAINE and any other oxidizing agents. Depending on the severity of the signs and symptoms, patients may respond to supportive care, i.e., oxygen therapy, hydration. A more severe clinical presentation may require treatment with methylene blue, exchange transfusion, or hyperbaric oxygen.

ADVERSE REACTIONS:

Systemic: The most commonly encountered acute adverse experiences that demand immediate countermeasures are related to the central nervous system and the cardiovascular system. These adverse experiences are generally dose related and may result from rapid absorption from the injection site, diminished tolerance, or from unintentional intravascular injection of the local anesthetic solution. In addition to systemic dose-related toxicity, unintentional subarachnoid injection of drug during the intended performance of caudal or lumbar epidural block or nerve blocks near the vertebral column (especially in the head and neck region) may result in underventilation or apnea (“Total Spinal”). Factors influencing plasma protein binding, such as acidosis, systemic diseases that alter protein production, or competition of other drugs for protein binding sites, may diminish individual tolerance. Plasma cholinesterase deficiency may also account for diminished tolerance to ester-type local anesthetics.

Central Nervous System Reactions: These are characterized by excitation and/or depression. Restlessness, anxiety, dizziness, tinnitus, blurred vision or tremors may occur, possibly proceeding to convulsions. However, excitement may be transient or absent, with depression being the first manifestation of an adverse reaction. This may quickly be followed by drowsiness merging into unconsciousness and respiratory arrest.

The incidence of convulsions associated with the use of local anesthetics varies with the procedure used and the total dose administered. In a survey of studies of epidural anesthesia, overt toxicity progressing to convulsions occurred in approximately 0.1 percent of local anesthetic administrations.

Cardiovascular System Reactions: High doses, or unintended intravascular injection, may lead to high plasma levels and related depression of the myocardium, hypotension, bradycardia, ventricular arrhythmias, and, possibly, cardiac arrest.

Allergic: Allergic type reactions are rare and may occur as a result of sensitivity to the local anesthetic or to other formulation ingredients, such as the antimicrobial preservative methylparaben, contained in multiple dose vials. These reactions are characterized by signs such as urticaria, pruritus, erythema, angioneurotic edema (including laryngeal edema), tachycardia, sneezing, nausea, vomiting, dizziness, syncope, excessive sweating, elevated temperature, and possibly, anaphylactoid type symptomatology (including severe hypotension). Cross sensitivity among members of the ester-type local anesthetic group has been reported. The usefulness of screening for sensitivity has not been definitely established.

Neurologic: In the practice of caudal or lumbar epidural block, occasional unintentional penetration of the subarachnoid space by the catheter may occur (see PRECAUTIONS). Subsequent adverse observations may depend partially on the amount of drug administered intrathecally. These observations may include spinal block of varying magnitude (including total spinal block), hypotension secondary to spinal block, loss of bladder and bowel control, and loss of perineal sensation and sexual function. Arachnoiditis, persistent motor, sensory and/or autonomic (sphincter control) deficit of some lower spinal segments with slow recovery (several months) or incomplete recovery have been reported in rare instances (see DOSAGE AND ADMINISTRATION discussion of Caudal and Lumbar Epidural Block). Backache and headache have also been noted following lumbar epidural or caudal block.

OVERDOSAGE:

Acute emergencies from local anesthetics are generally related to high plasma levels encountered during therapeutic use of local anesthetics or to unintended subarachnoid injection of local anesthetic solution (see ADVERSE REACTIONS, WARNINGS and PRECAUTIONS).

In mice, the intravenous LD50 of chloroprocaine HCl is 97 mg/kg and the subcutaneous LD 50 of chloroprocaine HCl is 950 mg/kg.

Management of Local Anesthetic Emergencies: The first consideration is prevention, best accomplished by careful and constant monitoring of cardiovascular and respiratory vital signs and the patient’s state of consciousness after each local anesthetic injection. At the first sign of change, oxygen should be administered.

The first step in the management of convulsions, as well as underventilation or apnea due to unintentional subarachnoid injection of drug solution, consists of immediate attention to the maintenance of a patent airway and assisted or controlled ventilation with oxygen and a delivery system capable of permitting immediate positive airway pressure by mask. Immediately after the institution of these ventilatory measures, the adequacy of the circulation should be evaluated, keeping in mind that drugs used to treat convulsions sometimes depress the circulation when administered intravenously. Should convulsions persist despite adequate respiratory support, and if the status of the circulation permits, small increments of an ultra-short acting barbiturate (such as thiopental or thiamylal) or a benzodiazepine (such as diazepam) may be administered intravenously; the clinician should be familiar, prior to the use of anesthetics, with these anticonvulsant drugs. Supportive treatment of circulatory depression may require administration of intravenous fluids and, when appropriate, a vasopressor dictated by the clinical situation (such as ephedrine to enhance myocardial contractile force).

If not treated immediately, both convulsions and cardiovascular depression can result in hypoxia, acidosis, bradycardia, arrhythmias and cardiac arrest. Underventilation or apnea due to unintentional subarachnoid injection of local anesthetic solution may produce these same signs and also lead to cardiac arrest if ventilatory support is not instituted. If cardiac arrest should occur, standard cardiopulmonary resuscitative measures should be instituted. Recovery has been reported after prolonged resuscitative efforts.

Endotracheal intubation, employing drugs and techniques familiar to the clinician, may be indicated, after initial administration of oxygen by mask, if difficulty is encountered in the maintenance of a patent airway or if prolonged ventilatory support (assisted or controlled) is indicated.

DOSAGE AND ADMINISTRATION:

Chloroprocaine may be administered as a single injection or continuously through an indwelling catheter. As with all local anesthetics, the dose administered varies with the anesthetic procedure, the vascularity of the tissues, the depth of anesthesia and degree of muscle relaxation required, the duration of anesthesia desired, and the physical condition of the patient. The smallest dose and concentration required to produce the desired result should be used. Dosage should be reduced for children, elderly and debilitated patients and patients with cardiac and/or liver disease. The maximum single recommended doses of chloroprocaine in adults are: without epinephrine, 11 mg/kg, not to exceed a maximum total dose of 800 mg; with epinephrine (1:200,000), 14 mg/kg, not to exceed a maximum total dose of 1000 mg. For specific techniques and procedures, refer to standard textbooks.

There have been adverse event reports of chondrolysis in patients receiving intra-articular infusions of local anesthetics following arthroscopic and other surgical procedures. Nesacaine is not approved for this use (see WARNINGS and DOSAGE AND ADMINISTRATION).

Caudal and Lumbar Epidural Block: In order to guard against adverse experiences sometimes noted following unintended penetration of the subarachnoid space, the following procedure modifications are recommended:

1. Use an adequate test dose (3 mL of Nesacaine-MPF 3% Injection or 5 mL of Nesacaine-MPF 2% Injection) prior to induction of complete block. This test dose should be repeated if the patient is moved in such a fashion as to have displaced the epidural catheter. Allow adequate time for onset of anesthesia following administration of each test dose.
2. Avoid the rapid injection of a large volume of local anesthetic injection through the catheter. Consider fractional doses, when feasible.
3. In the event of the known injection of a large volume of local anesthetic injection into the subarachnoid space, after suitable resuscitation and if the catheter is in place, consider attempting the recovery of drug by draining a moderate amount of cerebrospinal fluid (such as 10 mL) through the epidural catheter.

As a guide for some routine procedures, suggested doses are given below:

1. Infiltration and Peripheral Nerve Block: NESACAINE or NESACAINE-MPF (chloroprocaine HCl Injection, USP)

2. Caudal and Lumbar Epidural Block: NESACAINE-MPF INJECTION.For caudal anesthesia, the initial dose is 15 to 25 mL of a 2% or 3% solution. Repeated doses may be given at 40 to 60 minute intervals.For lumbar epidural anesthesia, 2 to 2.5 mL per segment of a 2% or 3% solution can be used. The usual total volume of Nesacaine-MPF Injection is from 15 to 25 mL. Repeated doses 2 to 6 mL less than the original dose may be given at 40 to 50 minute intervals.The above dosages are recommended as a guide for use in the average adult. Maximum dosages of all local anesthetics must be individualized after evaluating the size and physical condition of the patient and the rate of systemic absorption from a particular injection site.

Pediatric Dosage: It is difficult to recommend a maximum dose of any drug for children, since this varies as a function of age and weight. For children over 3 years of age who have a normal lean body mass and normal body development, the maximum dose is determined by the child’s age and weight and should not exceed 11 mg/kg (5 mg/lb). For example, in a child of 5 years weighing 50 lbs (23 kg), the dose of chloroprocaine HCl without epinephrine would be 250 mg. Concentrations of 0.5 to 1% are suggested for infiltration and 1 to 1.5% for nerve block. In order to guard against systemic toxicity, the lowest effective concentration and lowest effective dose should be used at all times. Some of the lower concentrations for use in infants and smaller children are not available in prepackaged containers; it will be necessary to dilute available concentrations with the amount of 0.9% sodium chloride injection necessary to obtain the required final concentration of chloroprocaine injection.

Preparation of Epinephrine Injections—To prepare a 1:200,000 epinephrine-chloroprocaine HCl injection, add 0.1 mL of a 1 to 1000 Epinephrine Injection USP to 20 mL of Nesacaine-MPF Injection.Chloroprocaine is incompatible with caustic alkalis and their carbonates, soaps, silver salts, iodine and iodides.

Parenteral drug products should be inspected visually for particulate matter and discoloration prior to administration, whenever injection and container permit. As with other anesthetics having a free aromatic amino group, Nesacaine and Nesacaine-MPF Injections are slightly photosensitive and may become discolored after prolonged exposure to light. It is recommended that these vials be stored in the original outer containers, protected from direct sunlight. Discolored injection should not be administered. If exposed to low temperatures, Nesacaine and Nesacaine-MPF Injections may deposit crystals of chloroprocaine HCl which will redissolve with shaking when returned to room temperature. The product should not be used if it contains undissolved (eg, particulate) material.

HOW SUPPLIED:

NESACAINE® (chloroprocaine HCL Injection, USP) with preservatives is supplied as follows:

NESACAINE®-MPF (chloroprocaine HCL Injection, USP) without preservatives and without EDTA is supplied as follows:

For single-dose vials: Discard unused portion.

Keep from freezing. Protect from light. Store at 20° to 25°C (68° to 77°F) [see USP Controlled Room Temperature].

All trademarks are the property of Fresenius Kabi USA, LLC.

Product repackaged by: Henry Schein, Inc., Bastian, VA 24314
From Original Manufacturer/Distributor's NDC and Unit of Sale | To Henry Schein Repackaged Product NDC and Unit of Sale | Total Strength/Total Volume (Concentration) per unit
NDC 63323-475-37 Unit of 25 | NDC 0404-9926-30 1 30 mL Multiple Dose Vial in a bag (Vial bears NDC 63323-475-01) | 1% (300 mg per 30 mL) (10 mg per mL)
NDC 63323-476-37 Unit of 25 | NDC 0404-9927-30 1 30 mL Multiple Dose Vial in a bag (Vial bears NDC 63323-476-01) | 2% (600 mg per 30 mL) (20 mg per mL)